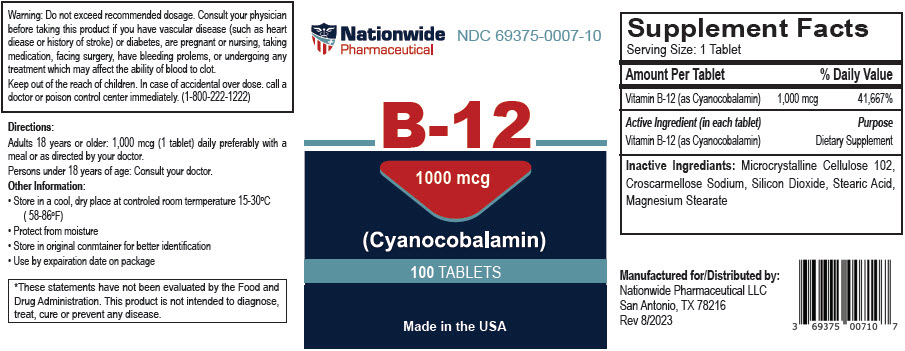 DRUG LABEL: B-12 (Cyanocobalamin)
NDC: 69375-007 | Form: TABLET
Manufacturer: Nationwide Pharmaceutical LLC
Category: other | Type: DIETARY SUPPLEMENT
Date: 20230803

ACTIVE INGREDIENTS: Cyanocobalamin 1000 ug/1 1
INACTIVE INGREDIENTS: Microcrystalline Cellulose 102; Croscarmellose sodium; Silicon Dioxide; Stearic Acid; Magnesium stearate

B-12 (Cyanocobalamin)

WARNINGS

Warning: Do not exceed recommended dosage. Consult your physician before taking this product if you have vascular disease (such as heart diease or history of stroke) or diabetes, are pregnant or nursing, taking medication, facing surgery, have bleeding prolems, or undergoing any treatment which may affect the ability of blood to clot.
Keep out of the reach of children. In case of accidental over dose. call a doctor or poison control center immediately. (1-800-222-1222)

Directions

Adults 18 years or older: 1,000 mcg (1 tablet) daily preferably with a meal or as directed by your doctor.

Persons under 18 years of age: Consult your doctor.

Other Information

- Store in a cool, dry place at controled room termperature 15-30°C (58-86°F)
- Protect from moisture
- Store in original conmtainer for better identification
- Use by expairation date on package

HEALTH CLAIM

*These statements have not been evaluated by the Food and Drug Administration. This product is not intended to diagnose, treat, cure or prevent any disease.

STATEMENT OF IDENTITY

Supplement Facts
Serving Size: 1 Tablet
Amount Per Tablet |  | % Daily Value
Vitamin B-12 (as Cyanocobalamin) | 1,000 mcg | 41,667%
Active Ingredient (in each tablet) |  | Purpose
Vitamin B-12 (as Cyanocobalamin) |  | Dietary Supplement
Inactive Ingrediants: Microcrystalline Cellulose 102, Croscarmellose Sodium, Silicon Dioxide, Stearic Acid, Magnesium Stearate

HEALTH CLAIM

Manufactured for/Distributed by:
Nationwide Pharmaceutical LLC
San Antonio, TX 78216
Rev 8/2023

PRINCIPAL DISPLAY PANEL - 1000 mcg Tablet Bottle Label

Nationwide
Pharmaceutical
NDC 69375-0007-10

B-12

1000 mcg

(Cyanocobalamin)

100 TABLETS

Made in the USA